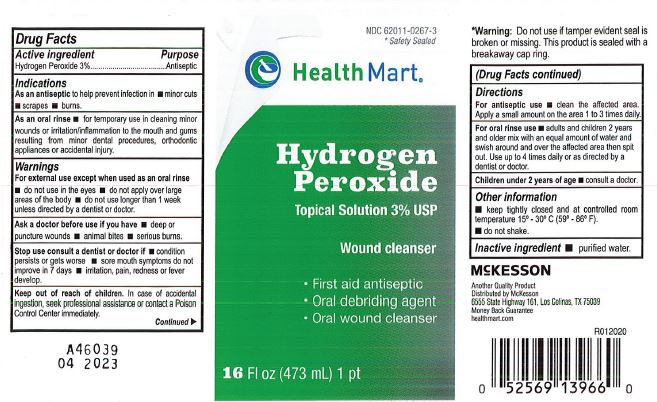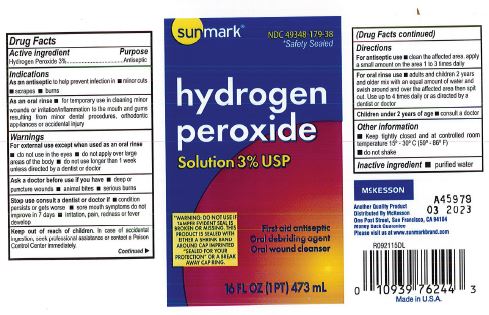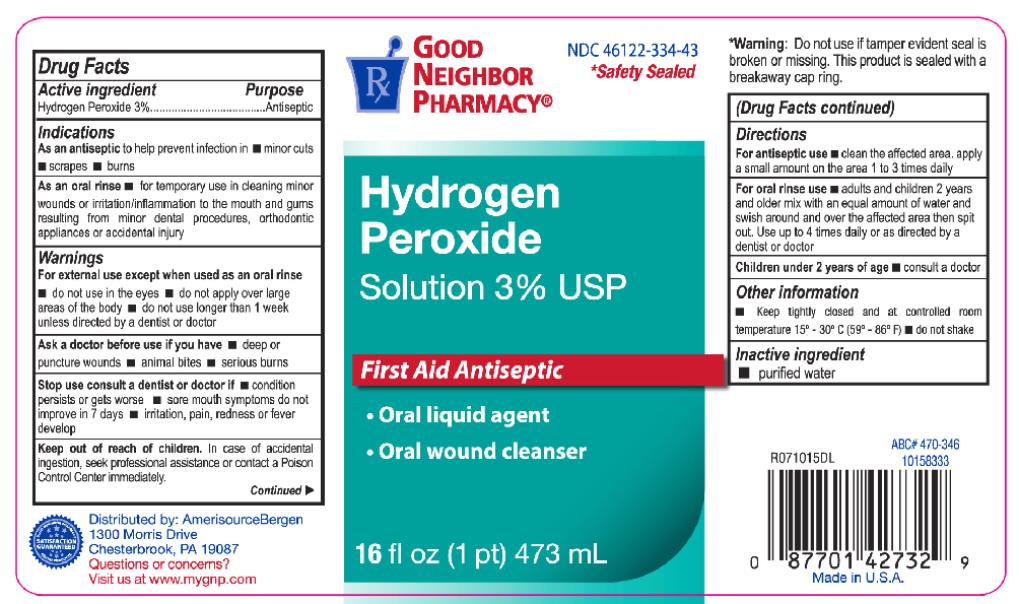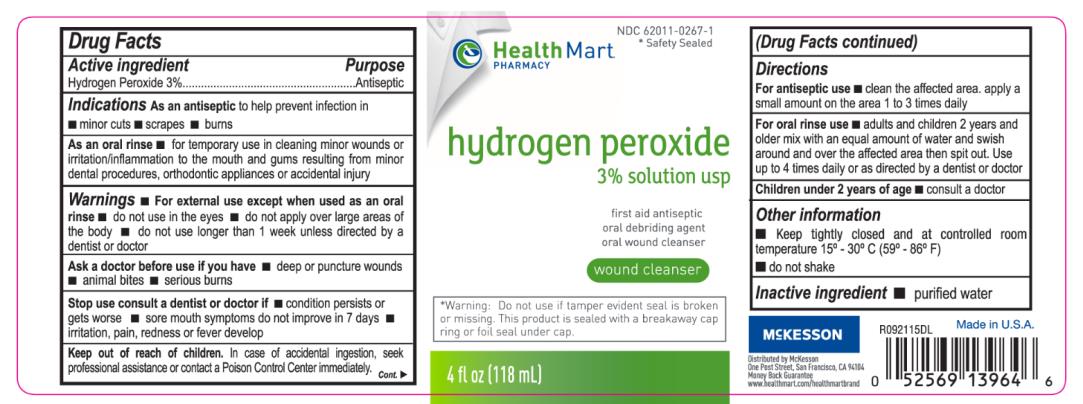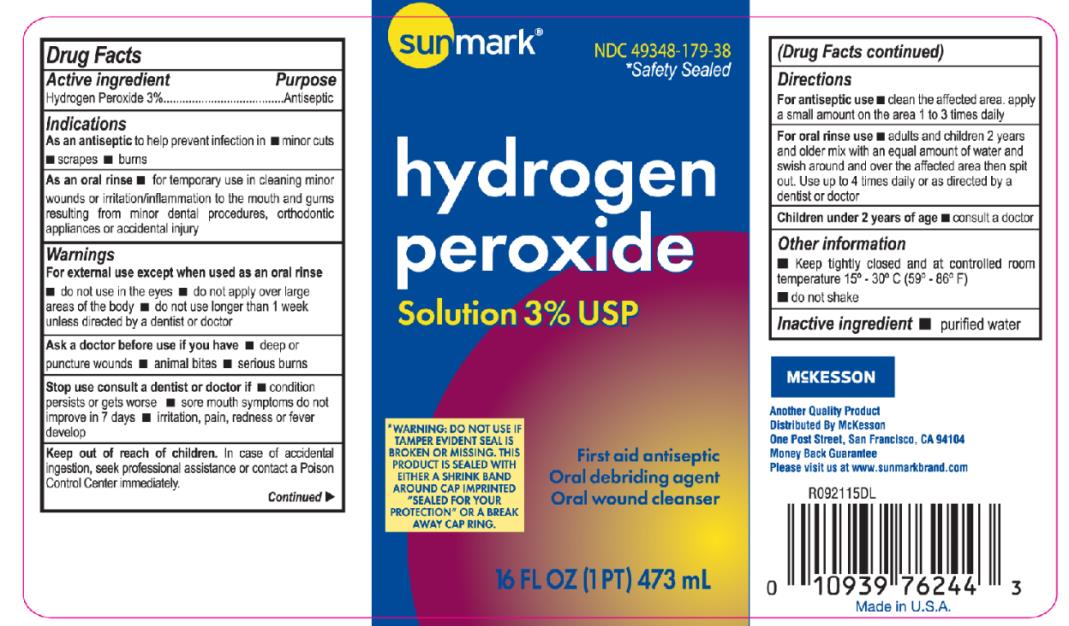 DRUG LABEL: Humco Hydrogen Peroxide
NDC: 82645-916 | Form: LIQUID
Manufacturer: Pharma Nobis, LLC
Category: otc | Type: HUMAN OTC DRUG LABEL
Date: 20231226

ACTIVE INGREDIENTS: HYDROGEN PEROXIDE 30 mg/1 mL
INACTIVE INGREDIENTS: WATER

Private Label Hydrogen Peroxide 3%, USP

Drug Facts

Active Ingredient

Hydrogen Peroxide 3%

Purpose

Antiseptic

Uses

As an antiseptic to help prevent infection in minor cuts, scrapes, burns.

As an oral rinse for temporary use in cleaning of minor wounds or irritation/inflammation to the mouth and gums resulting from minor dental procedures, orthodontic appliances or accidental injury.

Warnings

For external use except when used as an oral rinse.

Do not use in the eyes.

Do not apply over large areas of the body.

Do not use longer than 1 week unless directed by a dentist or doctor.

Ask a doctor before use if you have:

deep or puncture wounds, animal bites, serious burns.

Stop use consult a dentist or doctor if:

condition persists or gets worse, sore mouth symptoms do not improve in 7 days, irritation, pain, redness or fever develop.

Keep out of reach of children.

In case of acciedntal ingestion, seek professional assistance or contact a Poison Control Center immediately.

Directions

For antiseptic use: Clean the affected area, apply a small amount on the area 1 to 3 times daily.

For oral rinse use: Adults and children 2 years and older mix with an equal amount of water and swish around and over the affected area then spit out. Use up to 4 times daily or as directed by a dentist or a doctor.

Children under 2 years of age: consult a doctor.

Other information

Keep tightly closed and at controlled room temperature 15-30C (59-86F).

Do not shake.

Inactive ingredient

Purified water